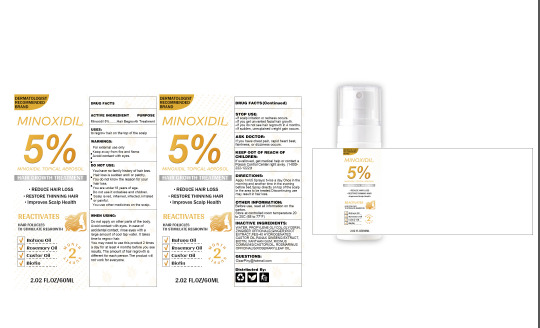 DRUG LABEL: MINOXIDIL TOPICAL
NDC: 83717-004 | Form: LIQUID
Manufacturer: Wenchang Panzhijie Trading Co., Ltd.
Category: otc | Type: HUMAN OTC DRUG LABEL
Date: 20240823

ACTIVE INGREDIENTS: MINOXIDIL 5 g/100 mL
INACTIVE INGREDIENTS: ROSEMARY OIL; GINGER; ASIAN GINSENG; CASTOR OIL; PROPYLENE GLYCOL; GLYCERIN; POLYOXYL 40 HYDROGENATED CASTOR OIL; BIOTIN; XANTHAN GUM; WATER

83717-004

ACTIVE INGREDIENT

Minoxidil 5%

Purpose

Hair Regrowth Treatment

Use

to regrow hair on the top of the scalp

Warnings

• For external use only

• Keep away from fire and flame

• Avoid contact with eyes

Do not use

• You have no family history of hair loss. Hair loss is sudden and/or patchy.

• You do not know the reason for your hair loss.

• You are under 18 years of age.

• Do not use it onbabies and children.Scalp is red, inflamed, infected, irritated or painful.

• You use other medicines on the scalp.

STOP USE AND SEE A DOCTOR

• If scalp irritation or redness occurs.

• If you get unwanted facial hair growth.

• If you do not see hair regrowth in 4 months.

• If sudden, unexplained weight gain occurs.

KEEP OUT OF REACH OF CHILDREN

If swallowed, get medical help or contact a Poison Control Center right away. (1-800-222-1222)

Directions

Apply 1ml(5 Sprays) twice a day.Once in the morning and another time in the evening before bed.

Spray directly on top of the scalp in the area to be treated.

Discontinuing use may result in hair loss.

Inactive ingredients

WATER, PROPYLENE GLYCOL, GLYCERIN, ZINGIBER OFFICINALE(GINGER)ROOT EXTRACT, PEG-40 HYDROGENATED CASTOR OIL, PANAX GINSENG EXTRACT, BIOTIN, XANTHAN GUM, RICINUS COMMUNIS(CASTOR)OIL, ROSMARINUS OFFICINALIS(ROSEMARY)LEAF OIL.